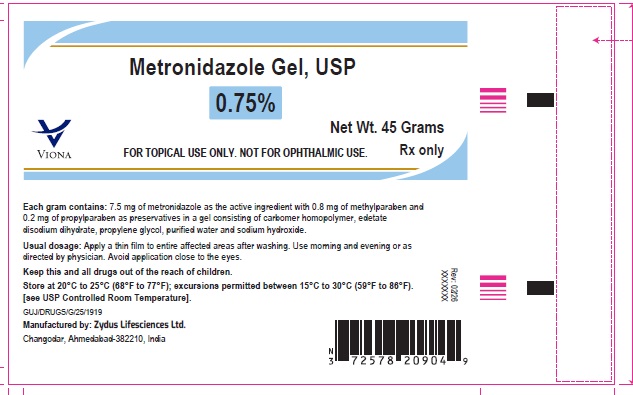 DRUG LABEL: Metronidazole
NDC: 70771-1978 | Form: GEL
Manufacturer: Zydus Lifesciences Limited
Category: prescription | Type: HUMAN PRESCRIPTION DRUG LABEL
Date: 20260219

ACTIVE INGREDIENTS: METRONIDAZOLE 7.5 mg/1 g
INACTIVE INGREDIENTS: CARBOMER HOMOPOLYMER TYPE C; EDETATE DISODIUM; METHYLPARABEN; PROPYLENE GLYCOL; PROPYLPARABEN; SODIUM HYDROXIDE; WATER

Metronidazole Gel USP, 0.75%

PACKAGE LABEL.PRINCIPAL DISPLAY PANEL

NDC 70771-1978-4

Metronidazole Gel USP, 0.75%

45 grams

Rx